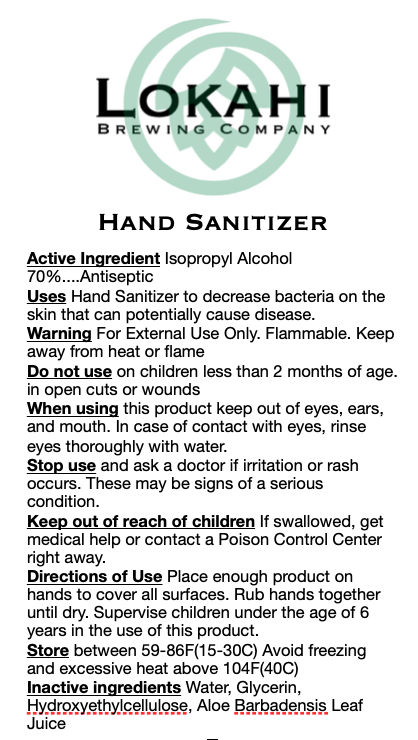 DRUG LABEL: Hand Sanitizer
NDC: 78240-001 | Form: GEL
Manufacturer: Lokahi Brewing Company LLC
Category: otc | Type: HUMAN OTC DRUG LABEL
Date: 20200619

ACTIVE INGREDIENTS: ISOPROPYL ALCOHOL 42 mL/100 mL
INACTIVE INGREDIENTS: ALOE ANDONGENSIS LEAF 0.3 mL/100 mL; GLYCERIN 2.4 mL/100 mL; HYDROXYETHYL CELLULOSE (100 MPA.S AT 2%) 0.9 mL/100 mL; WATER 24 mL/100 mL

Hand Sanitizer

The hand sanitizer is manufactured using only the following United States Pharmacopoeia (USP) grade ingredients.

1. Isopropyl Alcohol (70%, v/v) in an aqueous solution denatured according to Alcohol and Tobacco Tax and Trade Bureau regulations in 27 CFR part 20.
2. Glycerin (4% v/v).
3. Hydroxyethylcellulose (1.5% v/v).
4. Aloe Barbadensis Leaf Juice (0.5% v/v).
5. Sterile distilled water or boiled cold water.

The firm does not add other active or inactive ingredients. Different or additional ingredients may impact the quality and potency of the product.

Active Ingredient(s)

Isopropyl Alcohol 70% v/v. Purpose: Antiseptic

Purpose

Antiseptic, Hand Sanitizer

Use

Hand Sanitizer to help reduce bacteria that potentially can cause disease. For use when soap and water are not available.

Warnings

For external use only. Flammable. Keep away from heat or flame

Do not use

- in children less than 2 months of age
- in open cuts or wounds

When using this product keep out of eyes, ears, and mouth. In case of contact with eyes, rinse eyes thoroughly with water.
Stop use and ask a doctor if irritation or rash occurs. These may be signs of a serious condition.
Keep out of reach of children. If swallowed, get medical help or contact a Poison Control Center right away.

Stop use and ask a doctor if irritation or rash occurs. These may be signs of a serious condition.

Keep out of reach of children. If swallowed, get medical help or contact a Poison Control Center right away.

Directions

- Place enough product on hands to cover all surfaces. Rub hands together until dry.
- Supervise children under 6 years of age when using this product to avoid swallowing.

Other information

- Store between 15-30C (59-86F)
- Avoid freezing and excessive heat above 40C (104F)

Inactive ingredients

glycerin, hydroxyethyl cellulose, Aloa Barbadensis, purified water USP

Package Label - Principal Display Panel

60 ml NDC: 78240-001-01